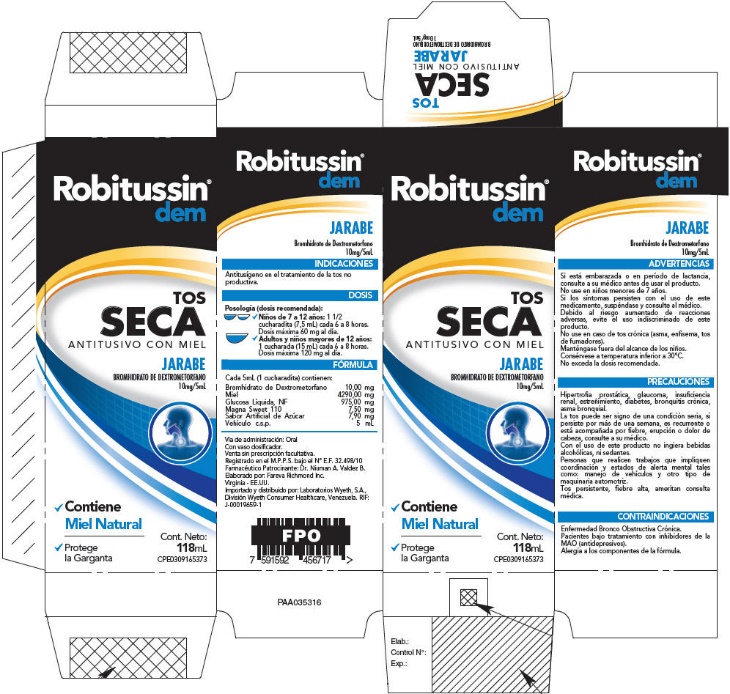 DRUG LABEL: Robitussin Tos Seca
NDC: 0031-8652 | Form: SYRUP
Manufacturer: Haleon US Holdings LLC
Category: otc | Type: HUMAN OTC DRUG LABEL
Date: 20240424

ACTIVE INGREDIENTS: DEXTROMETHORPHAN HYDROBROMIDE 10 mg/5 mL
INACTIVE INGREDIENTS: DEXTROSE, UNSPECIFIED FORM; GLYCERIN; METHYLPARABEN; HONEY; PROPYLENE GLYCOL; SODIUM BENZOATE; WATER

PRINCIPAL DISPLAY PANEL - 118 mL Bottle Carton

Robitussin®
dem

TOS
SECA
ANTITUSIVO CON MIEL

JARABE
BROMHIDRATO DE DEXTROMETORFANO
10mg/5mL

- Contiene
  Miel Natural
- Protege
  la Garganta

Cont. Neto:
118mL
CPE0309165373